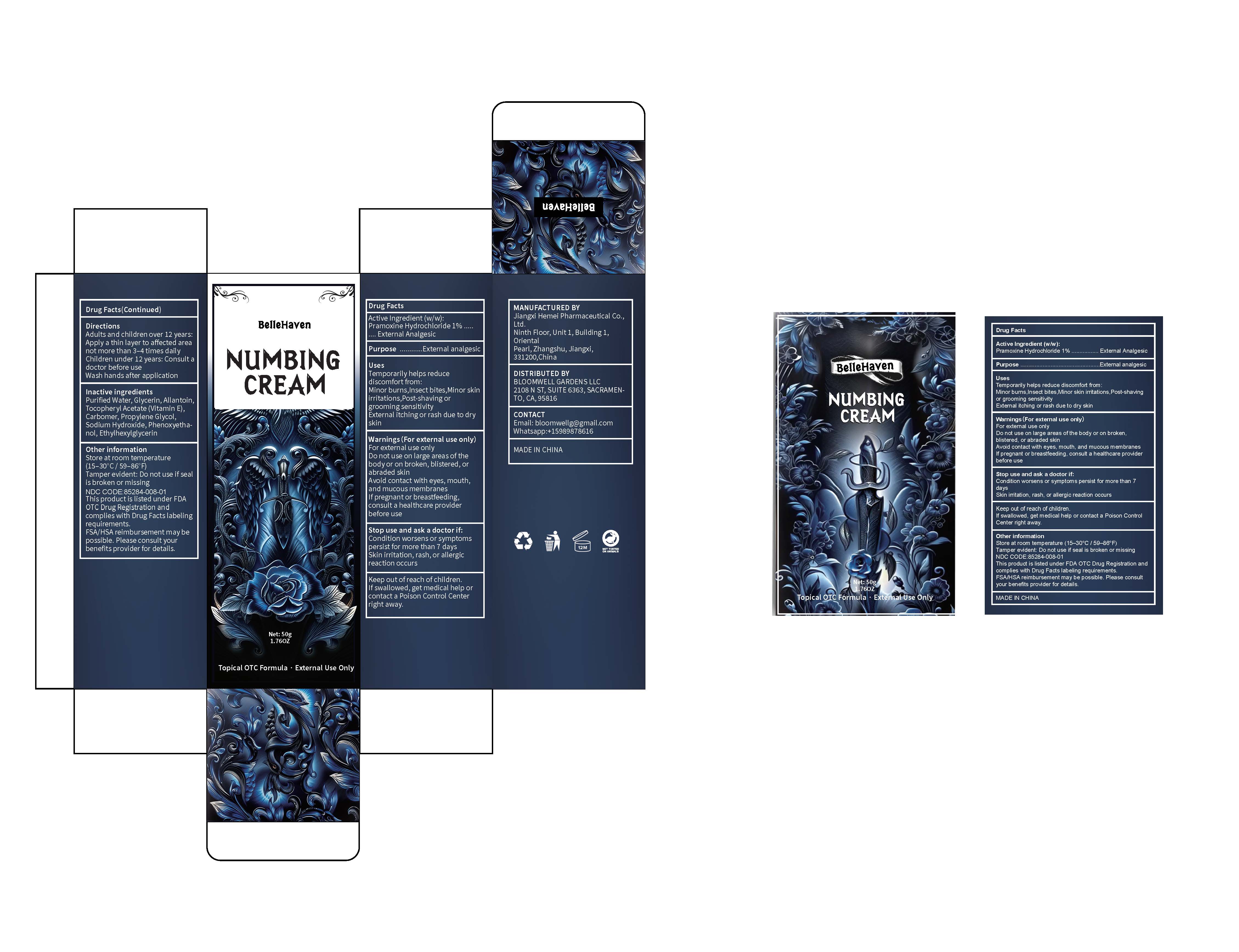 DRUG LABEL: Numbing cream
NDC: 85284-008 | Form: CREAM
Manufacturer: BLOOMWELL GARDENS LLC
Category: otc | Type: HUMAN OTC DRUG LABEL
Date: 20250813

ACTIVE INGREDIENTS: PRAMOXINE HYDROCHLORIDE 1 g/100 g
INACTIVE INGREDIENTS: PHENOXYETHANOL; ETHYLHEXYLGLYCERIN; ALLANTOIN; WATER; CARBOMER; GLYCERIN; VITAMIN E POLYETHYLENE GLYCOL SUCCINATE; SODIUM HYDROXIDE; PROPYLENE GLYCOL

Active Ingredient (w/w): Pramoxine Hydrochloride 1% ....External Analgesic

Inactive ingredients
Purified Water, Glycerin, Allantoin, Tocopheryl Acetate (Vitamin E), Carbomer, Propylene Glycol, Sodium Hydroxide, Phenoxyethanol, Ethylhexylglycerin

Purpose ............External analgesic

Uses

Temporarily helps reduce discomfort from:

Minor burns, Insect bites, Minor skin irritations, Post-shaving or grooming sensitivity

External itching or rash due to dry skin

Warnings (For external use only)
For external use only

Do not use on large areas of the body or on broken, blistered, or abraded skin
Avoid contact with eyes, mouth and mucous membranes
If pregnant or breast feeding, consult a healthcare provider before use

Stop use and ask a doctor if:
Condition worsens or symptoms persist for more than 7 days
Skin irritation, rash, or allergic reaction occurs

Keep out of reach of children.
If swallowed, get medical help or contact a Poison Control Center right away.

DOSAGE AND ADMINISTRATION

Adults and children over 12 years:
Apply a thin layer to affected area
not more than 3-4 times daily
Children under 12 years: Consult a doctor before use
Wash hands after application

OTHER SAFETY INFORMATION

Store at room temperature (15-30°C/59-86'F)

Tamper evident: Do not use if seal is broken or missing